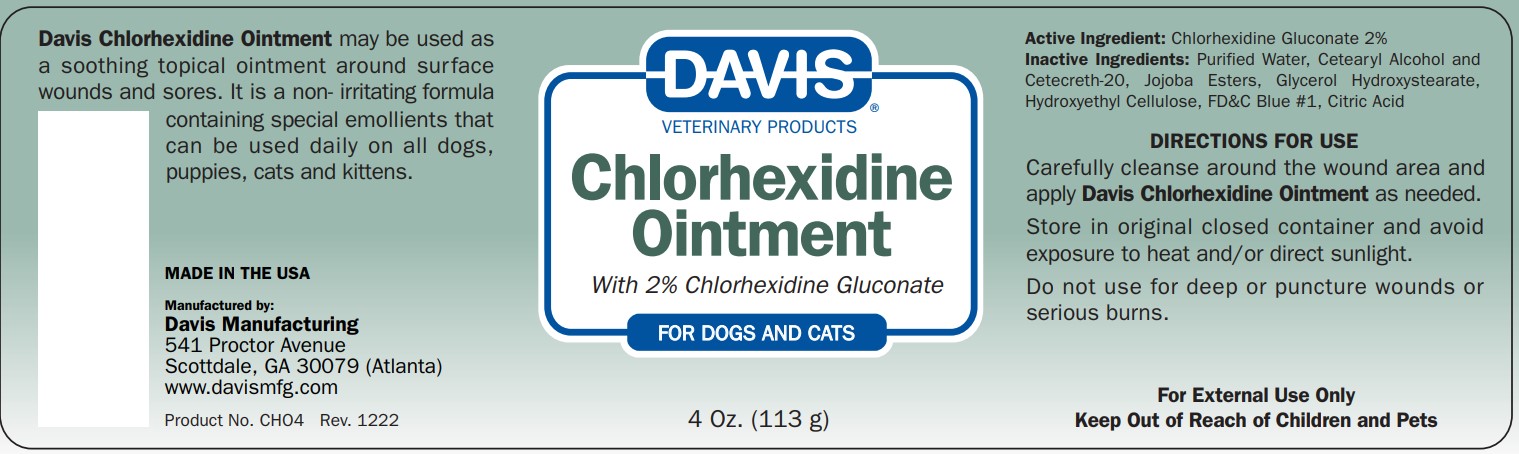 DRUG LABEL: Davis
NDC: 62570-020 | Form: OINTMENT
Manufacturer: Davis Manufacturing and Packaging Inc
Category: animal | Type: OTC ANIMAL DRUG LABEL
Date: 20230504

ACTIVE INGREDIENTS: CHLORHEXIDINE GLUCONATE 2 g/100 g
INACTIVE INGREDIENTS: water; FD&C BLUE NO. 1; HYDROXYETHYL CELLULOSE (4000 MPA.S AT 1%); POLYOXYL 20 CETOSTEARYL ETHER; CETOSTEARYL ALCOHOL; HYDROGENATED JOJOBA OIL/JOJOBA OIL, RANDOMIZED (IODINE VALUE 57-61); ANHYDROUS CITRIC ACID; PROPYLENE GLYCOL HYDROXYSTEARATE

Davis Chlorhexidine Ointment

DESCRIPTION

Davis Chlorhexidine Ointment may be used as
a soothing topical ointment around surface
wounds and sores. It is a non- irritating formula
containing special emollients that
can be used daily on all dogs,
puppies, cats and kittens.

Directions for Use
Carefully cleanse around the wound area and
apply Davis Chlorhexidine Ointment as needed.
Store in original closed container and avoid
exposure to heat and/or direct sunlight.
Do not use for deep or puncture wounds or
serious burns.

STORAGE AND HANDLING

Store in original closed container and avoid exposure to heat and/ or direct sunlight.

Do not use for deep or puncture wounds or serious burns.

For External Use Only
Keep Out of Reach of Children and Pets

ACTIVE INGREDIENT

Inactive Ingredients: Purified Water, Cetearyl Alcohol and
Cetecreth-20, Jojoba Esters, Glycerol Hydroxystearate,
Hydroxyethyl Cellulose, FD&C Blue #1, Citric Acid

MADE IN THE USA
Manufactured by:
Davis Manufacturing
541 Proctor Avenue
Scottdale, GA 30079 (Atlanta)
www.davismfg.com
Product No. CHO4 Rev. 1222

PACKAGE LABEL

Davis Veterinary Products

Chlorhexidine Ointment

with 2% Chlorhexidine Gluconate

For Dogs and Cats

4Oz. (113g)